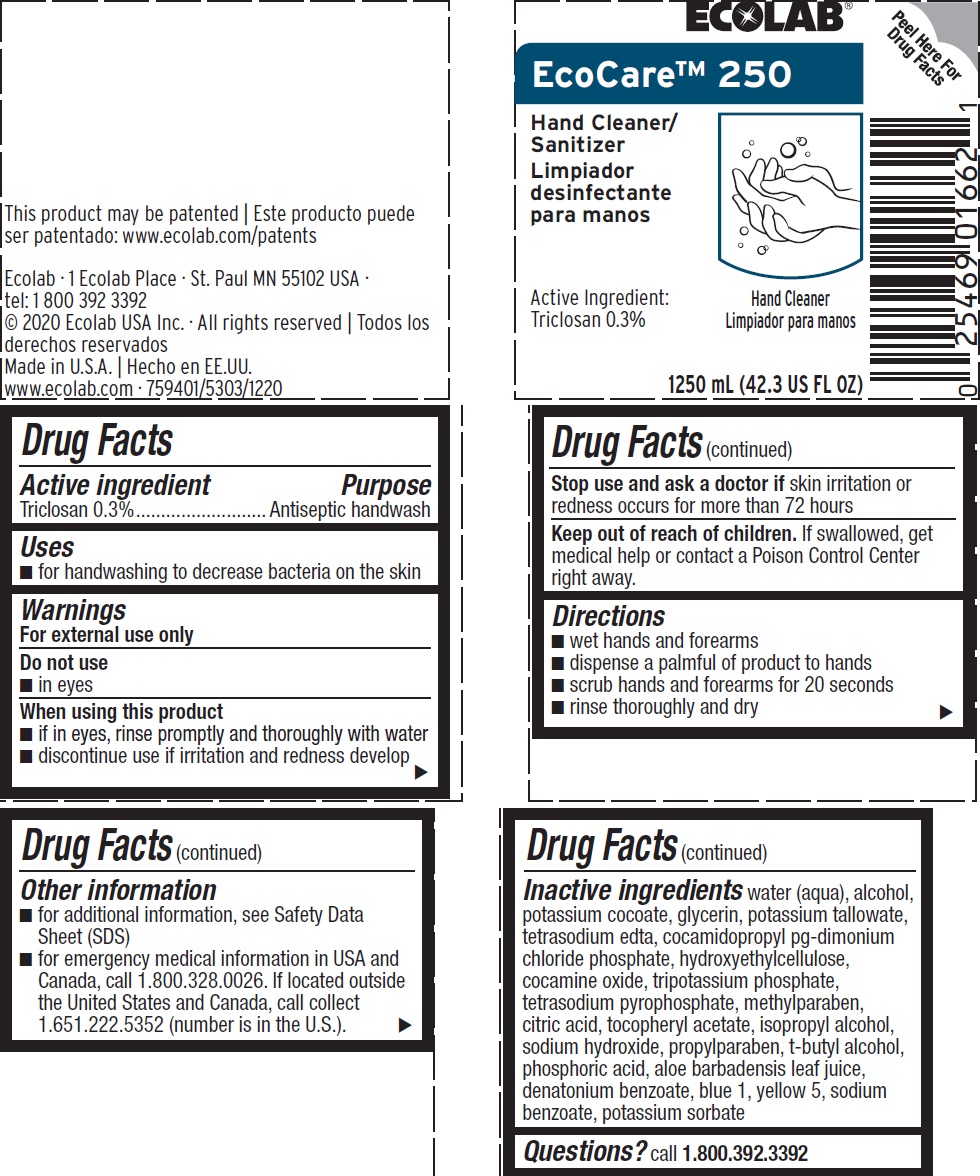 DRUG LABEL: EcoCare 250
NDC: 47593-360 | Form: SOLUTION
Manufacturer: Ecolab Inc.
Category: otc | Type: HUMAN OTC DRUG LABEL
Date: 20240321

ACTIVE INGREDIENTS: Triclosan 3 mg/1 mL
INACTIVE INGREDIENTS: WATER; ALCOHOL; POTASSIUM COCOATE; TALLOW ACID, BEEF; EDETATE SODIUM; COCAMIDOPROPYL PG-DIMONIUM CHLORIDE PHOSPHATE; HYDROXYETHYL CELLULOSE (3000 MPA.S AT 1%); COCAMINE OXIDE; POTASSIUM PHOSPHATE, TRIBASIC; SODIUM PYROPHOSPHATE; METHYLPARABEN; .ALPHA.-TOCOPHEROL ACETATE; CITRIC ACID MONOHYDRATE; ISOPROPYL ALCOHOL; SODIUM HYDROXIDE; PROPYLPARABEN; TERT-BUTYL ALCOHOL; PHOSPHORIC ACID; ALOE VERA LEAF; DENATONIUM BENZOATE; FD&C BLUE NO. 1; FD&C YELLOW NO. 5

Drug Facts

Active ingredient

Triclosan, 0.3%

Purpose

Antiseptic handwash

Uses

- for handwashing to decrease bacteria on the skin

Warnings

For external use only

Do not use

- in eyes

When using this product

- if in eyes, rinse promptly and thoroughly with water
- discontinue use if irritation and redness develop

Stop use and ask doctor if skin irritation or redness occurs for more than 72 hours

Keep out of reach of children. If swallowed, get medical help or contact a Poison Control Center right away.

Directions

- wet hands and forearms
- dispense a palmful of product to hands
- scrub hand and forearms for 20 seconds
- rinse thoroughly and dry

Other information

- for additional information, see Safety Data Sheet (SDS)
- for emergency medical information in USA and Canada, call 1.800.328.0026. If located outside the United States or Canada, call collect 1.651.222.5352 (number in U.S.)

INACTIVE INGREDIENT

Inactive Ingredients: water (aqua), alcohol, potassium cocoate, glycerin, potassium tallowate, tetrasodium edta, cocamidopropyl pg-dimonium chloride phosphate, hydroxyethylcellulose, cocamine oxide, tripotassium phosphate, tetrasodium pyrophosphate, methylparaben, citric acid, tocopheryl acetate, isopropyl alcohol, sodium hydroxide, propylparaben, t-butyl alcohol, phosphoric acid, aloe barbadensis leaf juice, denatonium benzoate, blue 1, yellow 5, sodium benzoate, potassium sorbate

Questions? call 1.800.392.3392

Representative label and principal display panel

ECOLAB

EcoCare 250

Hand Cleaner/Sanitizer

Active Ingredient:

Triclosan 0.3%

1250 mL (42.3 US FL OZ)

This product may be patented

www.ecolab.com/patents

Ecolab Inc. - 1 Ecolab Place - St. Paul, MN 55102 USA -

tel. 1 800 392 3392

©2020 Ecolab USA Inc. - All rights reserved

Made in U.S.A.

www.ecolab.com - 759401/5303/1220